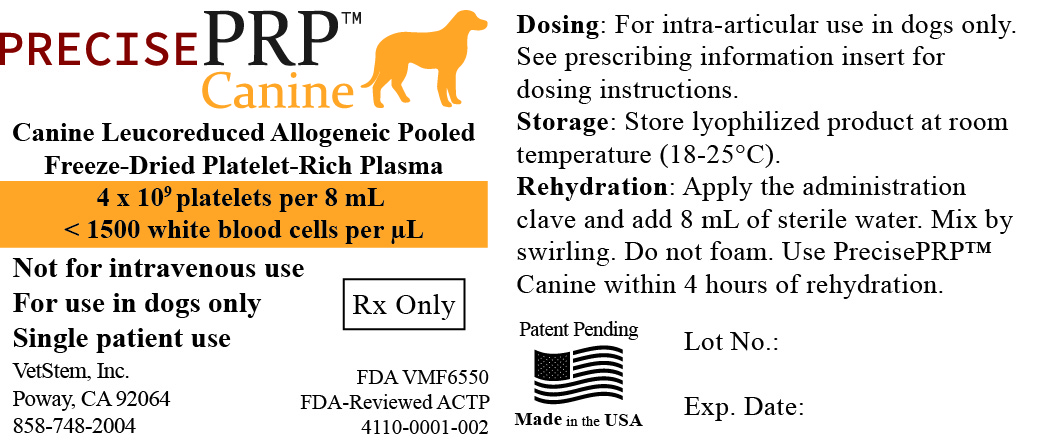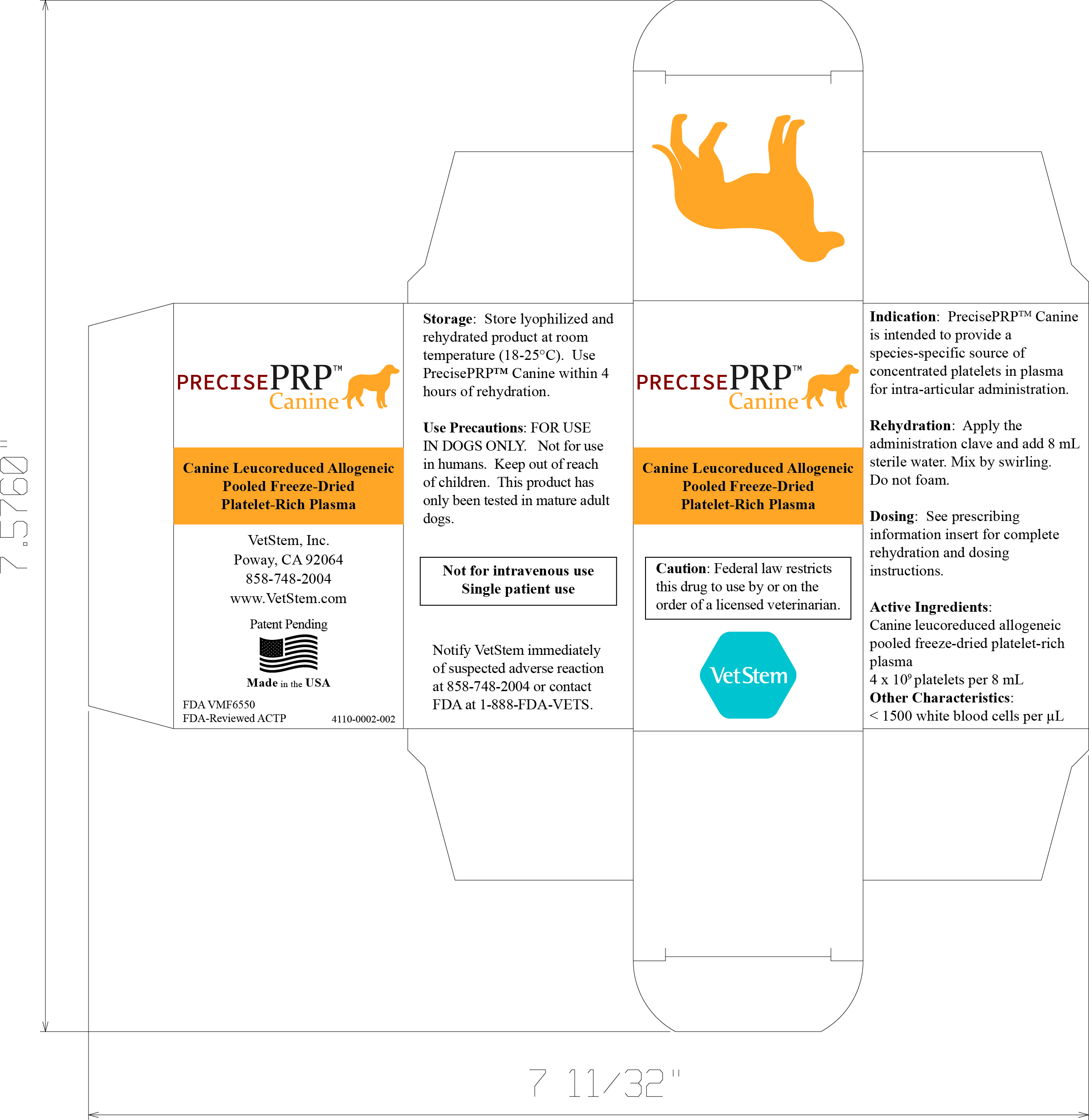 DRUG LABEL: PrecisePRP Canine
NDC: 86198-112 | Form: INJECTION, POWDER, FOR SUSPENSION
Manufacturer: VetStem,Inc
Category: other | Type: ANIMAL CELLS, TISSUES, AND CELL AND TISSUE BASED PRODUCT LABEL
Date: 20240507

ACTIVE INGREDIENTS: CANINE ALLOGENEIC FREEZE-DRIED PLATELET-RICH PLASMA 400000000 1/1 mL

Caution:

Federal (USA) law restricts this drug to use by or on the order of a licensed veterinarian.

Description:

PrecisePRP™ Canine is a leucoreduced allogeneic, pooled, freeze-dried platelet-rich plasma product from up to 36 canine donors. The biological source material for this product is in-date, apheresis-derived canine platelet concentrates leucoreduced to less than 1500 white blood cells per µL and apheresis-derived or whole blood-derived frozen plasma. Plasma antibody to DEA 1.1, 3, 4, 5, and 7 have been tested in all donors. Donors are selected and evaluated for infectious disease in accordance with FDA CVM Guidance #254. Supplied in a 50 mL glass vial, this product is a sterile, nonpyrogenic white-to-tan powder. Once rehydrated with 8 mL of sterile water for injection, this product is a light yellow translucent fluid with 4.0 x 109 platelets per vial and less than 1500 white blood cells per µL.

Indications:

PrecisePRP™ Canine is intended to provide a species-specific source of concentrated platelets in plasma for intra-articular administration.

Dosage & Administration:

PrecisePRP™ Canine is for intra-articular administration only. One vial provides 8 mL of allogeneic pooled platelet-rich plasma with a total of approximately 4 x 109 canine platelets per vial and less than 1500 white blood cells per µL. Do not mix this product with other products or solutions. Use according to Table 1 and adjust the dose based on the size of the dog and the joint being treated.
Rehydration Instructions (Perform Aseptically):
• Draw 8 milliliters of sterile water into a sterile syringe and needle.
• Apply the supplied vented administration clave to the PrecisePRP™ Canine vial and firmly seat it on the crimped seal.
• Disengage the needle and, using sterile technique, attach the syringe to the clave hub.
• Slowly add the sterile water down the side of the vial lumen to avoid foaming and immerse the cake in the rehydrating fluid.
• Gently mix the fluid and the lyophilized powder by swirling the vial to rehydrate.
• Draw into a syringe using the bidirectional clave.
• Engage a needle greater than or equal to 22 gauge for administration.
• Store at room temperature (18-25℃) until administration for not more than four (4) hours.
• Discard the excess product.

Dosage:

Dosage is lesion dependent and determined by the practitioner at the time of use. Each microliter of PrecisePRP™ Canine contains 500,000 +/- 100,000 platelets and less than 1500 white blood cells. The dose given may be adjusted based on the size of the dog and the joint being injected. The following table is a general guide to dosing based upon literature references.

Joint Small Dog 1-20 kg Large Dog >20 kg
Small Joint (i.e., tarsus, carpus) 0.5 mL 2.0 mL
Large Joint (i.e., stifle, hip) 1.0 mL 2.0 mL

Contraindications:

Do not use in dogs with known hypersensitivity to PrecisePRP™ Canine.

Warnings:

For use in dogs only. Not for use in humans. Keep out of reach of children. Rehydrated PrecisePRP™ Canine should be used within 4 hours of rehydration.

Precautions:

PrecisePRP™ Canine has only been tested in mature adult dogs.
PrecisePRP™ Canine has not been evaluated in breeding, pregnant, or lactating dogs.
PrecisePRP™ Canine is not intended for intravenous administration.

Adverse Reactions:

PrecisePRP™ Canine is made using platelets and plasma from up to 32 canine donors and, as with all blood products, has a risk of infectious disease. Donor maintenance includes routine screening for pathogens by PCR and ELISA testing.
In a randomized, placebo-controlled study of 12 laboratory beagles, PrecisePRP™ Canine was tested at the label dose of 2 mL per joint in two consecutive joint injections two weeks apart. There were no adverse treatment-related effects on body weights, gait, daily health observations, temperature, pulse, respiration, clinical pathology, injection sites, no significant findings on veterinary physical exams, and no adverse events as a result of treatment.
Published safety data exists for both canine and equine allogeneic platelet-rich plasma. Clinical case reports, systemic literature reviews, preclinical safety analysis, and comparative studies with autologous platelet-rich plasma and mesenchymal stem cells are available for the horse and dog. In the safety evaluation published by Garbin[1], a pooled allogeneic freeze-dried PRP was evaluated with autologous frozen products for safety and found to be statistically unremarkable from autologous products relating to inflammation and lameness post injection. In an Italian clinical trial in canine patients, no adverse events associated with immunogenicity were noted utilizing a pooled allogeneic platelet-rich plasma[2].
Report any suspected adverse reactions associated with the use of PrecisePRP™ Canine to VetStem Customer Service by calling 858-748-2004. For additional information about adverse drug experience reporting animal drugs, contact FDA at 1-888-FDA-VETS or visit www.fda.gov/animalveterinary/safetyhealth.

Information for Dog Owners:

Owners of patients should be made aware of the use of allogeneic blood products and their possible side effects. Adverse reactions may include joint pain for several days following injection, transient inflammation and swelling in the injected joint, joint infections, and transmission of disease agents from donor animals.

Clinical Pharmacology:

Platelet-rich plasma has been studied in multiple species with varying use profiles. A thorough review of the literature yielded over 30 references in support of platelet-rich plasma and its use as a topical, intra-articular and/or intralesional therapy published since 2008. Meta-analysis in human clinical trials as well as multiple study reviews in canine and equine suggest that the most common concern for platelet-rich plasma effectiveness is associated with a lack of uniformity and standardization[3, 4]. Important components of platelet-rich plasma have been debated; however, total platelet dose, growth factor content, and leucocyte count appear to be common factors for most authors when relating in vitro characterization and effectiveness outcomes[5]. Review of the veterinary literature was used to support both potential indications as well as dose and administration.
Platelets are provided to supply the growth factors and cytokines located in the alpha granules. After administration, the growth factors and cytokines are released into the area of injection and provide anti-inflammatory cytokines and repair signaling. Platelets also release factors that attract mesenchymal stem cells, leucocytes, and other mononuclear immune cells to assist in the repair process. It has been reported that PRP injected reduces pain signaling.
Recently, the discussion of platelet phenotypes and their relationships to platelet function, circulation, and membrane characteristic have led to the exploration of new methods for platelet concentrate storage, including storage at 4-8℃. Current published uses of platelet-rich plasma in the canine and equine support that it can be used intra-articularly, intralesionally, or topically and should be activated to allow the release of dense and alpha granules. Cold-stored platelets have been characterized as moderately activated as compared to room temperature-stored platelets. Recent in vitro characterization of the cold-stored platelets supports that their phenotype is most consistent with the desired function of platelet-rich plasma[6]. Manipulating the storage parameter for platelet concentrates prior to pooling and lyophilization allows platelet lyophilization without cryopreservatives (VetStem pilot data, 2022).

References:

1. Garbin, L.C., et al., A safety evaluation of allogeneic freeze-dried platelet-rich plasma or conditioned serum compared to autologous frozen products equivalents in equine healthy joints. BMC Vet Res, 2022. 18(1): p. 141.
2. Catarino, J., et al., Treatment of canine osteoarthritis with allogeneic platelet-rich plasma: review of five cases. Open Vet J, 2020. 10(2): p. 226-231.
3. Everts, P.A., et al., Modifying Orthobiological PRP Therapies Are Imperative for the Advancement of Treatment Outcomes in Musculoskeletal Pathologies. Biomedicines, 2022. 10(11).
4. Garbin LC, et al., (2021), A Critical Overview of the Use of Platelet-Rich Plasma in Equine Medicine Over the Last Decade. Front. Vet. Sci. 8:641818.
5. McCarrel, T. and L. Fortier, Temporal growth factor release from platelet-rich plasma, trehalose lyophilized platelets, and bone marrow aspirate and their effect on tendon and ligament gene expression. J Orthop Res, 2009. 27(8): p. 1033-42.
6. Zhao, H.Q., et al., Cold-stored platelets are effective in an in vitro model of massive transfusion protocol assessed by rotational thromboelastometry. Transfusion, 2022. 62 Suppl 1: p. S53-S62.

PrecisePRP™ is a trademark of VetStem, Inc.
 2024 VetStem, Inc.

Patent Pending
Revised 30Jan2024
6135-0001-002